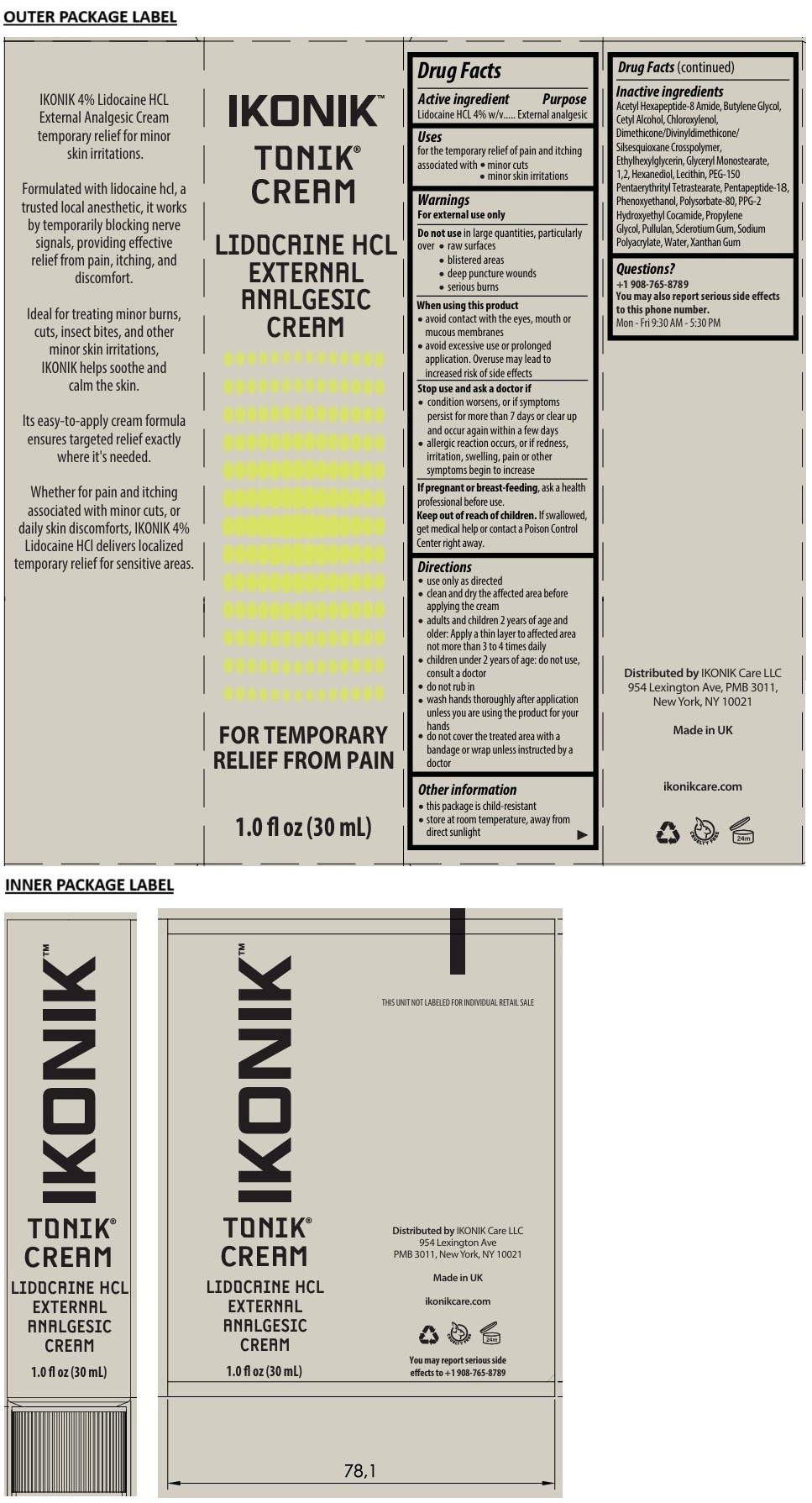 DRUG LABEL: IKONIK TONIK
NDC: 85132-001 | Form: CREAM
Manufacturer: IKONIK CARE, LLC
Category: otc | Type: HUMAN OTC DRUG LABEL
Date: 20250114

ACTIVE INGREDIENTS: LIDOCAINE HYDROCHLORIDE 4 g/100 mL
INACTIVE INGREDIENTS: ACETYL HEXAPEPTIDE-8 AMIDE; BUTYLENE GLYCOL; CETYL ALCOHOL; CHLOROXYLENOL; DIMETHICONE/DIVINYLDIMETHICONE/SILSESQUIOXANE CROSSPOLYMER; ETHYLHEXYLGLYCERIN; GLYCERYL MONOSTEARATE; 1,2-HEXANEDIOL; SOYBEAN LECITHIN; PEG-150 PENTAERYTHRITYL TETRASTEARATE; PENTAPEPTIDE-18; PHENOXYETHANOL; POLYSORBATE 80; PPG-2 HYDROXYETHYL COCAMIDE; PROPYLENE GLYCOL; PULLULAN; BETASIZOFIRAN; SODIUM POLYACRYLATE (8000 MW); WATER; XANTHAN GUM

IKONIK™ TONIK® CREAM LIDOCAINE HCL EXTERNAL ANALGESIC CREAM

Active ingredient

Lidocaine HCL 4% w/v

Purpose

External analgesic

Uses

for the temporary relief of pain and itching associated with • minor cuts • minor skin irritations

Warnings

For external use only

Do not use in large quantities, particularly over • raw surfaces • blistered areas • deep puncture wounds • serious burns

When using this product
• avoid contact with the eyes, mouth or mucous membranes
• avoid excessive use or prolonged application. Overuse may lead to increased risk of side effects

Stop use and ask a doctor if
• condition worsens, or if symptoms persist for more than 7 days or clear up and occur again within a few days
• allergic reaction occurs, or if redness, irritation, swelling, pain or other symptoms begin to increase

If pregnant or breast-feeding, ask a health professional before use.

Keep out of reach of children. If swallowed, get medical help or contact a Poison Control Center right away.

Directions

• use only as directed
• clean and dry the affected area before applying the cream
• adults and children 2 years of age and older: Apply a thin layer to affected area not more than 3 to 4 times daily
• children under 2 years of age: do not use, consult a doctor
• do not rub in
• wash hands thoroughly after application unless you are using the product for your hands
• do not cover the treated area with a bandage or wrap unless instructed by a doctor

Other information

• this package is child-resistant
• store at room temperature, away from direct sunlight

Inactive ingredients

Acetyl Hexapeptide-8 Amide, Butylene Glycol, Cetyl Alcohol, Chloroxylenol, Dimethicone/Divinyldimethicone/Silsesquioxane Crosspolymer, Ethylhexylglycerin, Glyceryl Monostearate, 1,2, Hexanediol, Lecithin, PEG-150 Pentaerythrityl Tetrastearate, Pentapeptide-18, Phenoxyethanol, Polysorbate-80, PPG-2 Hydroxyethyl Cocamide, Propylene Glycol, Pullulan, Sclerotium Gum, Sodium Polyacrylate, Water, Xanthan Gum

Questions?

+1 908-765-8789
You may also report serious side effects to this phone number.
Mon - Fri 9:30 AM - 5:30 PM

FOR TEMPORARY RELIEF FROM PAIN

IKONIK 4% Lidocaine HCL External Analgesic Cream temporary relief for minor skin irritations.

Formulated with lidocaine hcl, a trusted local anesthetic, it works by temporarily blocking nerve signals, providing effective relief from pain, itching, and discomfort.

Ideal for treating minor burns, cuts, insect bites, and other minor skin irritations, IKONIK helps soothe and calm the skin.

Its easy-to-apply cream formula ensures targeted relief exactly where it's needed.

Whether for pain and itching associated with minor cuts, or daily skin discomforts, IKONIK 4% Lidocaine HCl delivers localized temporary relief for sensitive areas.

THIS UNIT NOT LABELED FOR INDIVIDUAL RETAIL SALE

Distributed by IKONIK Care LLC
954 Lexington Ave,
PMB 3011, New York, NY 10021

Made in UK

ikonikcare.com

CRUELTY FREE